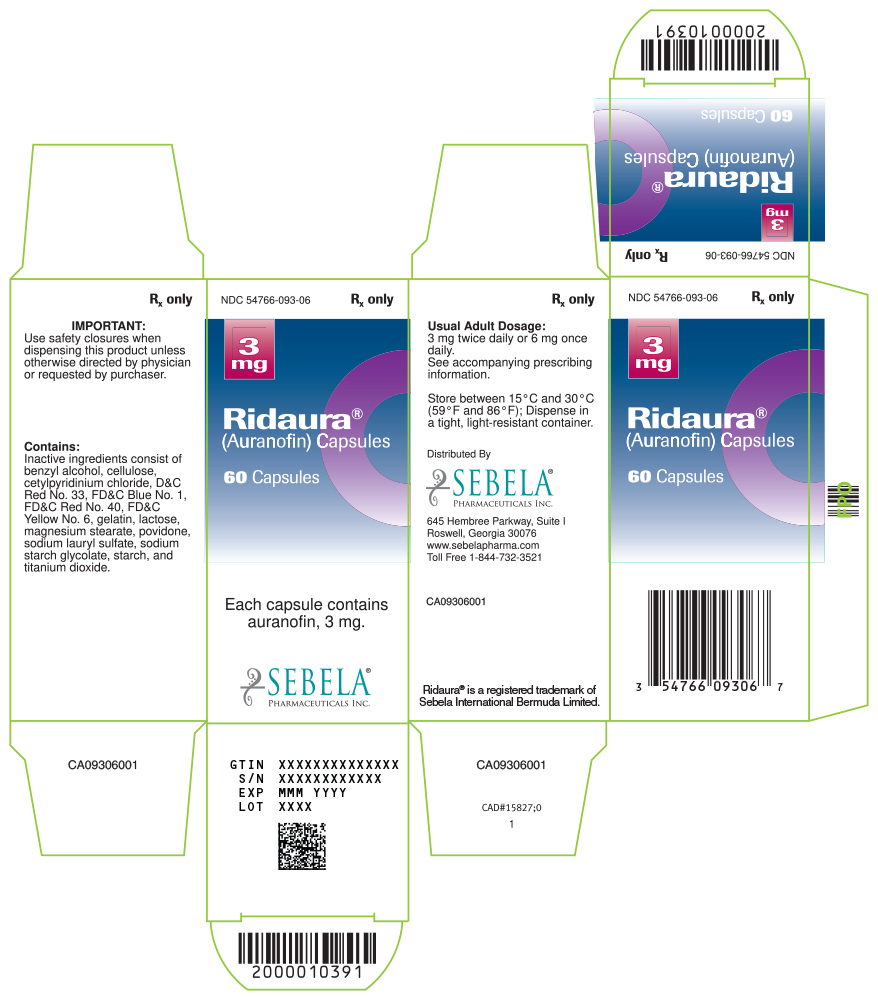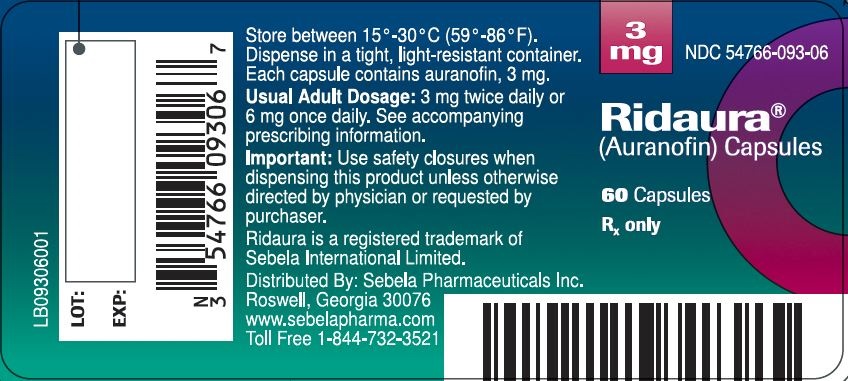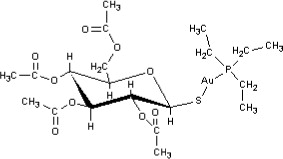 DRUG LABEL: RIDAURA
NDC: 54766-093 | Form: CAPSULE
Manufacturer: Sebela Pharmaceuticals Inc.
Category: prescription | Type: HUMAN PRESCRIPTION DRUG LABEL
Date: 20251108

ACTIVE INGREDIENTS: AURANOFIN 3 mg/1 1
INACTIVE INGREDIENTS: BENZYL ALCOHOL; CELLULOSE, MICROCRYSTALLINE; CETYLPYRIDINIUM CHLORIDE; D&C RED NO. 33; FD&C BLUE NO. 1; FD&C RED NO. 40; FD&C YELLOW NO. 6; GELATIN; LACTOSE; MAGNESIUM STEARATE; POVIDONE; SODIUM LAURYL SULFATE; SODIUM STARCH GLYCOLATE TYPE A POTATO; STARCH, CORN; TITANIUM DIOXIDE

PRESCRIBING INFORMATION
RIDAURA®
Auranofin
Capsules

Rx Only

BOXED WARNING

RIDAURA® (auranofin) contains gold and, like other gold-containing drugs, can cause gold toxicity, signs of which include: fall in hemoglobin, leukopenia below 4,000 WBC/cu mm, granulocytes below 1,500/cu mm, decrease in platelets below 150,000/cu mm, proteinuria, hematuria, pruritus, rash, stomatitis or persistent diarrhea. Therefore, the results of recommended laboratory work (See PRECAUTIONS) should be reviewed before writing each RIDAURA prescription. Like other gold preparations, RIDAURA is only indicated for use in selected patients with active rheumatoid arthritis. Physicians planning to use RIDAURA should be experienced with chrysotherapy and should thoroughly familiarize themselves with the toxicity and benefits of RIDAURA.

In addition, the following precautions should be routinely employed:

1. The possibility of adverse reactions should be explained to patients before starting therapy.
2. Patients should be advised to report promptly any symptoms suggesting toxicity. (See PRECAUTIONS—Information for Patients.)

DESCRIPTION

RIDAURA (auranofin) is available in oral form as capsules containing 3 mg auranofin.

Auranofin is (2,3,4,6-tetra-O-acetyl-1-thio-ß-D-glucopyranosato-S-) (triethyl–phosphine) gold.

Auranofin contains 29% gold and has the following chemical structure:

Each RIDAURA capsule, with opaque brown cap and opaque tan body, contains auranofin, 3 mg, and is imprinted with the product name RIDAURA. Inactive ingredients consist of benzyl alcohol, cellulose, cetylpyridinium chloride, D&C Red No. 33, FD&C Blue No. 1, FD&C Red No. 40, FD&C Yellow No. 6, gelatin, lactose, magnesium stearate, povidone, sodium lauryl sulfate, sodium starch glycolate, starch, titanium dioxide and trace amounts of other inactive ingredients.

CLINICAL PHARMACOLOGY

The mechanism of action of RIDAURA (auranofin) is not understood. In patients with adult rheumatoid arthritis, RIDAURA may modify disease activity as manifested by synovitis and associated symptoms, and reflected by laboratory parameters such as ESR. There is no substantial evidence, however, that gold-containing compounds induce remission of rheumatoid arthritis.

PHARMACOKINETICS

Pharmacokinetics: Pharmacokinetic studies were performed in rheumatoid arthritis patients, not in normal volunteers. Auranofin is rapidly metabolized and intact auranofin has never been detected in the blood. Thus, studies of the pharmacokinetics of auranofin have involved measurement of gold concentrations. Approximately 25% of the gold in auranofin is absorbed.

The mean terminal plasma half-life of auranofin gold at steady state was 26 days (range 21 to 31 days; n=5). The mean terminal body half-life was 80 days (range 42 to 128; n=5). Approximately 60% of the absorbed gold (15% of the administered dose) from a single dose of auranofin is excreted in urine; the remainder is excreted in the feces.

In clinical studies, steady state blood-gold concentrations are achieved in about three months. In patients on 6 mg auranofin/day, mean steady state blood-gold concentrations were 0.68 ±0.45 mcg/mL (n=63 patients). In blood, approximately 40% of auranofin gold is associated with red cells, and 60% associated with serum proteins. In contrast, 99% of injectable gold is associated with serum proteins.

Mean blood-gold concentrations are proportional to dose; however, no correlation between blood-gold concentrations and safety or efficacy has been established.

INDICATIONS AND USAGE

RIDAURA (auranofin) is indicated in the management of adults with active classical or definite rheumatoid arthritis (ARA criteria) who have had an insufficient therapeutic response to, or are intolerant of, an adequate trial of full doses of one or more nonsteroidal anti-inflammatory drugs. RIDAURA should be added to a comprehensive baseline program, including non-drug therapies.

Unlike anti-inflammatory drugs, RIDAURA does not produce an immediate response. Therapeutic effects may be seen after three to four months of treatment, although improvement has not been seen in some patients before six months.

When cartilage and bone damage has already occurred, gold cannot reverse structural damage to joints caused by previous disease. The greatest potential benefit occurs in patients with active synovitis, particularly in its early stage.

In controlled clinical trials comparing RIDAURA with injectable gold, RIDAURA was associated with fewer dropouts due to adverse reactions, while injectable gold was associated with fewer dropouts for inadequate or poor therapeutic effect. Physicians should consider these findings when deciding on the use of RIDAURA in patients who are candidates for chrysotherapy.

CONTRAINDICATIONS

RIDAURA (auranofin) is contraindicated in patients with a history of any of the following gold-induced disorders: anaphylactic reactions, necrotizing enterocolitis, pulmonary fibrosis, exfoliative dermatitis, bone marrow aplasia or other severe hematologic disorders.

WARNINGS

Danger signs of possible gold toxicity include fall in hemoglobin, leukopenia below 4,000 WBC/cu mm, granulocytes below 1,500/cu mm, decrease in platelets below 150,000/cu mm, proteinuria, hematuria, pruritus, rash, stomatitis or persistent diarrhea.

Thrombocytopenia has occurred in 1–3% of patients (See ADVERSE REACTIONS) treated with RIDAURA (auranofin), some of whom developed bleeding. The thrombocytopenia usually appears to be peripheral in origin and is usually reversible upon withdrawal of RIDAURA. Its onset bears no relationship to the duration of RIDAURA therapy and its course may be rapid. While patients' platelet counts should normally be monitored at least monthly (See PRECAUTIONS— Laboratory Tests), the occurrence of a precipitous decline in platelets or a platelet count less than 100,000/cu mm or signs and symptoms (e.g., purpura, ecchymoses or petechiae) suggestive of thrombocytopenia indicates a need to immediately withdraw RIDAURA and other therapies with the potential to cause thrombocytopenia, and to obtain additional platelet counts. No additional RIDAURA should be given unless the thrombocytopenia resolves and further studies show it was not due to gold therapy.

Proteinuria has developed in 3-9% of patients (See ADVERSE REACTIONS) treated with RIDAURA. If clinically significant proteinuria or microscopic hematuria is found (See PRECAUTIONS— Laboratory Tests), RIDAURA and other therapies with the potential to cause proteinuria or microscopic hematuria should be stopped immediately.

PRECAUTIONS

GENERAL PRECAUTIONS

General: The safety of concomitant use of RIDAURA (auranofin) with injectable gold, hydroxychloroquine, penicillamine, immunosuppressive agents (e.g., cyclophosphamide, azathioprine, or methotrexate) or high doses of corticosteroids has not been established.

Medical problems that might affect the signs or symptoms used to detect RIDAURA toxicity should be under control before starting RIDAURA (auranofin).

The potential benefits of using RIDAURA in patients with progressive renal disease, significant hepatocellular disease, inflammatory bowel disease, skin rash or history of bone marrow depression should be weighed against 1) the potential risks of gold toxicity on organ systems previously compromised or with decreased reserve, and 2) the difficulty in quickly detecting and correctly attributing the toxic effect.

The following adverse reactions have been reported with the use of gold preparations and require modification of RIDAURA treatment or additional monitoring. See ADVERSE REACTIONS for the approximate incidence of those reactions specifically reported with RIDAURA.

Gastrointestinal Reactions: Gastrointestinal reactions reported with gold therapy include diarrhea/loose stools, nausea, vomiting, anorexia and abdominal cramps. The most common reaction to RIDAURA is diarrhea/ loose stools reported in approximately 50% of the patients. This is generally manageable by reducing the dosage (e.g., from 6 mg daily to 3 mg) and in only 6% of the patients is it necessary to discontinue RIDAURA (auranofin) permanently. Ulcerative enterocolitis is a rare serious gold reaction. Therefore, patients with gastrointestinal symptoms should be monitored for the appearance of gastrointestinal bleeding.

Cutaneous Reactions: Dermatitis is the most common reaction to injectable gold therapy and the second most common reaction to RIDAURA. Any eruption, especially if pruritic, that develops during treatment should be considered a gold reaction until proven otherwise. Pruritus often exists before dermatitis becomes apparent, and therefore should be considered to be a warning signal of a cutaneous reaction. Gold dermatitis may be aggravated by exposure to sunlight or an actinic rash may develop. The most serious form of cutaneous reaction reported with injectable gold is generalized exfoliative dermatitis.

Mucous Membrane Reactions: Stomatitis, another common gold reaction, may be manifested by shallow ulcers on the buccal membranes, on the borders of the tongue, and on the palate or in the pharynx. Stomatitis may occur as the only adverse reaction or with a dermatitis. Sometimes diffuse glossitis or gingivitis develops. A metallic taste may precede these oral mucous membrane reactions and should be considered a warning signal.

Renal Reactions: Gold can produce a nephrotic syndrome or glomerulitis with proteinuria and hematuria. These renal reactions are usually relatively mild and subside completely if recognized early and treatment is discontinued. They may become severe and chronic if treatment is continued after the onset of the reaction. Therefore it is important to perform urinalyses regularly and to discontinue treatment promptly if proteinuria or hematuria develops.

Hematologic Reactions: Blood dyscrasias including leukopenia, granulocytopenia, thrombocytopenia and aplastic anemia have all been reported as reactions to injectable gold and RIDAURA. These reactions may occur separately or in combination at anytime during treatment. Because they have potentially serious consequences, blood dyscrasias should be constantly watched for through regular monitoring (at least monthly) of the formed elements of the blood throughout treatment.

Miscellaneous Reactions: Rare reactions attributed to gold include cholestatic jaundice; gold bronchitis and interstitial pneumonitis and fibrosis; peripheral neuropathy; partial or complete hair loss; fever.

PATIENT COUNSELING INFORMATION

Information for Patients: Patients should be advised of the possibility of toxicity from RIDAURA and of the signs and symptoms that they should report promptly. (Patient information sheets are available.)

Women of childbearing potential should be warned of the potential risks of RIDAURA therapy during pregnancy (See PRECAUTIONS— Pregnancy).

LABORATORY TESTS

Laboratory Tests: CBC with differential, platelet count, urinalysis, and renal and liver function tests should be performed prior to RIDAURA (auranofin) therapy to establish a baseline and to identify any preexisting conditions.

CBC with differential, platelet count and urinalysis should then be monitored at least monthly; other parameters should be monitored as appropriate.

DRUG INTERACTIONS

Drug Interactions: In a single patient-report, there is the suggestion that concurrent administration of RIDAURA and phenytoin may have increased phenytoin blood levels.

CARCINOGENESIS AND MUTAGENESIS AND IMPAIRMENT OF FERTILITY

Carcinogenesis/Mutagenesis: In a 24-month study in rats, animals treated with auranofin at 0.4, 1.0 or 2.5 mg/kg/day orally (3, 8 or 21 times the human dose) or gold sodium thiomalate at 2 or 6 mg/kg injected twice weekly (4 or 12 times the human dose) were compared to untreated control animals.

There was a significant increase in the frequency of renal tubular cell karyomegaly and cytomegaly and renal adenoma in the animals treated with 1.0 or 2.5 mg/kg/day of auranofin and 2 or 6 mg/kg twice weekly of gold sodium thiomalate. Malignant renal epithelial tumors were seen in the 1.0 mg/kg/day and the 2.5 mg/kg/day auranofin and in the 6 mg/kg twice weekly gold sodium thiomalate–treated animals.

In a 12-month study, rats treated with auranofin at 23 mg/kg/day (192 times the human dose) developed tumors of the renal tubular epithelium, whereas those treated with 3.6 mg/ kg/day (30 times the human dose) did not.

In an 18-month study in mice given oral auranofin at doses of 1, 3 and 9 mg/kg/day (8, 24 and 72 times the human dose), there was no statistically significant increase above controls in the instances of tumors.

In the mouse lymphoma forward mutation assay, auranofin at high concentrations (313 to 700 ng/mL) induced increases in the mutation frequencies in the presence of a rat liver microsomal preparation. Auranofin produced no mutation effects in the Ames test (Salmonella), in the in vitro assay (Forward and Reverse Mutation Inducement Assay with Saccharomyces), in the in vitro transformation of BALB/T3 cell mouse assay or in the Dominant Lethal Assay.

PREGNANCY

Pregnancy: Teratogenic Effects— Pregnancy Category C. Use of RIDAURA (auranofin) by pregnant women is not recommended. Furthermore, women of childbearing potential should be warned of the potential risks of RIDAURA therapy during pregnancy. (See below.)

Pregnant rabbits given auranofin at doses of 0.5, 3 or 6 mg/kg/day (4.2 to 50 times the human dose) had impaired food intake, decreased maternal weights, decreased fetal weights and an increase above controls in the incidence of resorptions, abortions and congenital abnormalities, mainly abdominal defects such as gastroschisis and umbilical hernia. Pregnant rats given auranofin at a dose of 5 mg/kg/day (42 times the human dose) had an increase above controls in the incidence of resorptions and a decrease in litter size and weight linked to maternal toxicity. No such effects were found in rats given 2.5 mg/kg/day (21 times the human dose).

Pregnant mice given auranofin at a dose of 5 mg/kg/day (42 times the human dose) had no teratogenic effects.

There are no adequate and well-controlled RIDAURA studies in pregnant women.

NURSING MOTHERS

Nursing Mothers: Nursing during RIDAURA therapy is not recommended.

Following auranofin administration to rats and mice, gold is excreted in milk. Following the administration of injectable gold, gold appears in the milk of nursing women; human data on auranofin are not available.

PEDIATRIC USE

Pediatric Use: RIDAURA (auranofin) is not recommended for use in pediatric patients because its safety and effectiveness have not been established.

ADVERSE REACTIONS

The adverse reactions incidences listed below are based on observations of 1) 4,784 RIDAURA treated patients in clinical trials (2,474 U.S., 2,310 foreign), of whom 2,729 were treated more than one year and 573 for more than three years; and 2) postmarketing experience. The highest incidence is during the first six months of treatment; however, reactions can occur after many months of therapy. With rare exceptions, all patients were on concomitant nonsteroidal anti-inflammatory therapy; some of them were also taking low dosages of corticosteroids.

Reactions occurring in more than 1% of RIDAURA-treated patients

Gastrointestinal: loose stools or diarrhea (47%); abdominal pain (14%); nausea with or without vomiting (10%); constipation; anorexia*; flatulence*; dyspepsia*; dysgeusia.

Dermatological: rash (24%); pruritus (17%); hair loss; urticaria.

Mucous Membrane: stomatitis (13%); conjunctivitis*; glossitis.

Hematological: anemia; leukopenia; thrombocytopenia; eosinophilia.

Renal: proteinuria*; hematuria.

Hepatic: elevated liver enzymes.

*Reactions marked with an asterisk occurred in 3-9% of the patients. The other reactions listed occurred in 1-3%.

Reactions occurring in less than 1% of RIDAURA-treated patients

Gastrointestinal: dysphagia; gastrointestinal bleeding†; melena†; positive stool for occult blood†; ulcerative enterocolitis.

Dermatological: angioedema.

Mucous Membrane: gingivitis†.

Hematological: aplastic anemia; neutropenia†; agranulocytosis; pure red cell aplasia; pancytopenia.

Hepatic: jaundice.

Respiratory: interstitial pneumonitis.

Neurological: peripheral neuropathy.

Ocular: gold deposits in the lens or cornea unassociated clinically with eye disorders or visual impairment.

† Reactions marked with a dagger occurred in 0.1-1% of the patients. The other reactions listed occurred in less than 0.1%.

Reactions reported with injectable gold preparations, but not with RIDAURA (auranofin) (based on clinical trials and on postmarketing experience)

Cutaneous Reactions: generalized exfoliative dermatitis

Incidence of Adverse Reactions for Specific Categories – 18 Comparative Trials
 | Ridaura (445 patients) | Injectable Gold (445 patients)
Proteinuria | 0.9% | 5.4%
Rash | 26% | 39%
Diarrhea | 42.5% | 13%
Stomatitis | 13% | 18%
Anemia | 3.1% | 2.7%
Leukopenia | 1.3% | 2.2%
Thromocytopenia | 0.9% | 2.2%
Elevated liver function tests | 1.9% | 1.7%
Pulmonary | 0.2% | 0.2%

OVERDOSAGE

The acute oral LD50 for auranofin is 310 mg/kg in adult mice and 265 mg/ kg in adult rats. The minimum lethal dose in rats is 30 mg/kg.

In case of acute overdosage, immediate induction of emesis or gastric lavage and appropriate supportive therapy are recommended.

RIDAURA overdosage experience is limited. A 50-year-old female, previously on 6 mg RIDAURA daily, took 27 mg (9 capsules) daily for 10 days and developed an encephalopathy and peripheral neuropathy. RIDAURA was discontinued and she eventually recovered.

There has been no experience with treating RIDAURA overdosage with modalities such as chelating agents. However, they have been used with injectable gold and may be considered for RIDAURA overdosage.

DOSAGE AND ADMINISTRATION

Usual Adult Dosage: The usual adult dosage of RIDAURA (auranofin) is 6 mg daily, given either as 3 mg twice daily or 6 mg once daily. Initiation of therapy at dosages exceeding 6 mg daily is not recommended because it is associated with an increased incidence of diarrhea. If response is inadequate after six months, an increase to 9 mg (3 mg three times daily) may be tolerated. If response remains inadequate after a three-month trial of 9 mg daily, RIDAURA therapy should be discontinued. Safety at dosages exceeding 9 mg daily has not been studied.

Transferring from Injectable Gold:

In controlled clinical studies, patients on injectable gold have been transferred to RIDAURA (auranofin) by discontinuing the injectable agent and starting oral therapy with RIDAURA, 6 mg daily. When patients are transferred to RIDAURA, they should be informed of its adverse reaction profile, in particular the gastrointestinal reactions. (See PRECAUTIONS— Information for Patients.) At six months, control of disease activity of patients transferred to RIDAURA and those maintained on the injectable agent was not different. Data beyond six months are not available.

HOW SUPPLIED

Capsules, containing 3 mg auranofin, in bottles of 60.

NDC 54766-093-06

STORAGE AND HANDLING

Store between 15° and 30°C (59° and 86°F). Dispense in a tight, light-resistant container.

©2018 Sebela Pharmaceuticals Inc.
All rights reserved.

RIDAURA is a registered trademark of Sebela International Limited

Distributed by:

Sebela Pharmaceuticals Inc.

645 Hembree Parkway, Suite I

Roswell, Georgia 30076

www.sebelapharma.com

Toll Free 1-844-732-3521

Revised October 2017

PI 09306001

Principal Display Panel – 3 mg Bottle Label

3 mg NDC 54766-093-06

Ridaura®
Auranofin Capsules

60 Capsules

PACKAGE LABEL

Principal Display Panel – 3 mg Carton

3 mg NDC 54766-093-06

Ridaura ®
Auranofin Capsules

60 Capsules